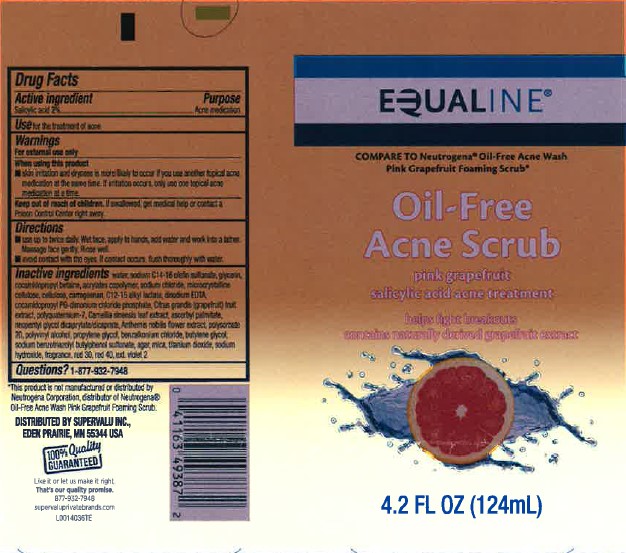 DRUG LABEL: Acne Scrub
NDC: 41163-821 | Form: GEL
Manufacturer: United Natural Foods, Inc. dba UNFI
Category: otc | Type: HUMAN OTC DRUG LABEL
Date: 20260217

ACTIVE INGREDIENTS: SALICYLIC ACID 20 mg/1 mL
INACTIVE INGREDIENTS: WATER; SODIUM C14-16 OLEFIN SULFONATE; GLYCERIN; COCAMIDOPROPYL BETAINE; BUTYL ACRYLATE/METHYL METHACRYLATE/METHACRYLIC ACID COPOLYMER (18000 MW); SODIUM CHLORIDE; MICROCRYSTALLINE CELLULOSE; POWDERED CELLULOSE; CARRAGEENAN; C12-15 ALKYL LACTATE; EDETATE DISODIUM ANHYDROUS; COCAMIDOPROPYL PROPYLENE GLYCOL-DIMONIUM CHLORIDE PHOSPHATE; PUMMELO; POLYQUATERNIUM-7 (70/30 ACRYLAMIDE/DADMAC; 1600 KD); GREEN TEA LEAF; ASCORBYL PALMITATE; NEOPENTYL GLYCOL DICAPRYLATE/DICAPRATE; CHAMAEMELUM NOBILE FLOWER; POLYSORBATE 20; POLYVINYL ALCOHOL, UNSPECIFIED; PROPYLENE GLYCOL; BENZALKONIUM CHLORIDE; BUTYLENE GLYCOL; SODIUM BENZOTRIAZOLYL BUTYLPHENOL SULFONATE; AGAR; MICA; TITANIUM DIOXIDE; SODIUM HYDROXIDE; D&C RED NO. 30; FD&C RED NO. 40; EXT. D&C VIOLET NO. 2

Equaline 821.002/821AD-AF
Acne Scrub Pink Grapefruit

Active ingredient

Salicylic acid 2%

Purpose

Acne medication

Use

for the treatment of acne

Warnings

For external use only

When using this product

- skin irritation and dryness is more likely to occur if you use another topical acne medication at the same time. If irritation occurs, only use one topical acne medication at a time.

Keep out of reach of children.

If swallowed, get medical help or contact a Poison Control Center right away.

Directions

- use up to twice daily. Wet face, apply to hands, add water and work into a lather. Massage face gently. Rinse well.
- avoid contact with the eyes. If contact occurs, flush thoroughly with water.

Inactive ingredients

water, sodium C14-16 olefin sulfonate, glycerin, cocamidopropyl betaine, acrylates copolymer, sodium chloride, microcrystalline cellulose, cellulose, carrageenan, C12-15 alkyl lactate, disodium EDTA, cocamidopropyl PG-dimonium chloride phosphate, Citrus grandis (grapefruit) fruit extract, polyquaternium-7, Camellia sinensis leaf extract, ascorbyl palmitate, neopentyl glycol dicaprylate/dicaprate, Anthemis nobilis flower extract, polysorbate 20, polyvinyl alcohol, propylene glycol, benzalkonium chloride, butylene glycol, sodium benzotriazolyl butylphenol sulfonate, agar, mica, titanium dioxide, sodium hydroxide, fragrance, red 30, red 40, ext. violet 2

Questions?

1-877-932-7948

Disclaimer

*This product is not manufactured or distributed by Neutrogena Corporation, distributor of NeutrogenaOil-Free Acne Wash Pink Grapefruit Foaming Scrub.

Adverse reactions

DISTRIBUTED BY SUPERVALU INC.,

EDEN PRAIRIE, MN 55344 USA

100% QUALITY GUARANTEED

Like it or let us make it right.

That's our quality promise.

877-932-7946

supervaluprivatebrands.com

Principal display panel

EQUALINE®

Compare to Neutrogena®Oil-Free Acne Wash Pink Grapefruit Foaming Scrub*

Oil-Free

Acne Scrub

Pink Grapefruit

Salicylic Acid Acne Treatment

Helps Fight Breakouts

Contains Naturally Derived Grapefruit Extract

4.2 FL OZ (124 mL)